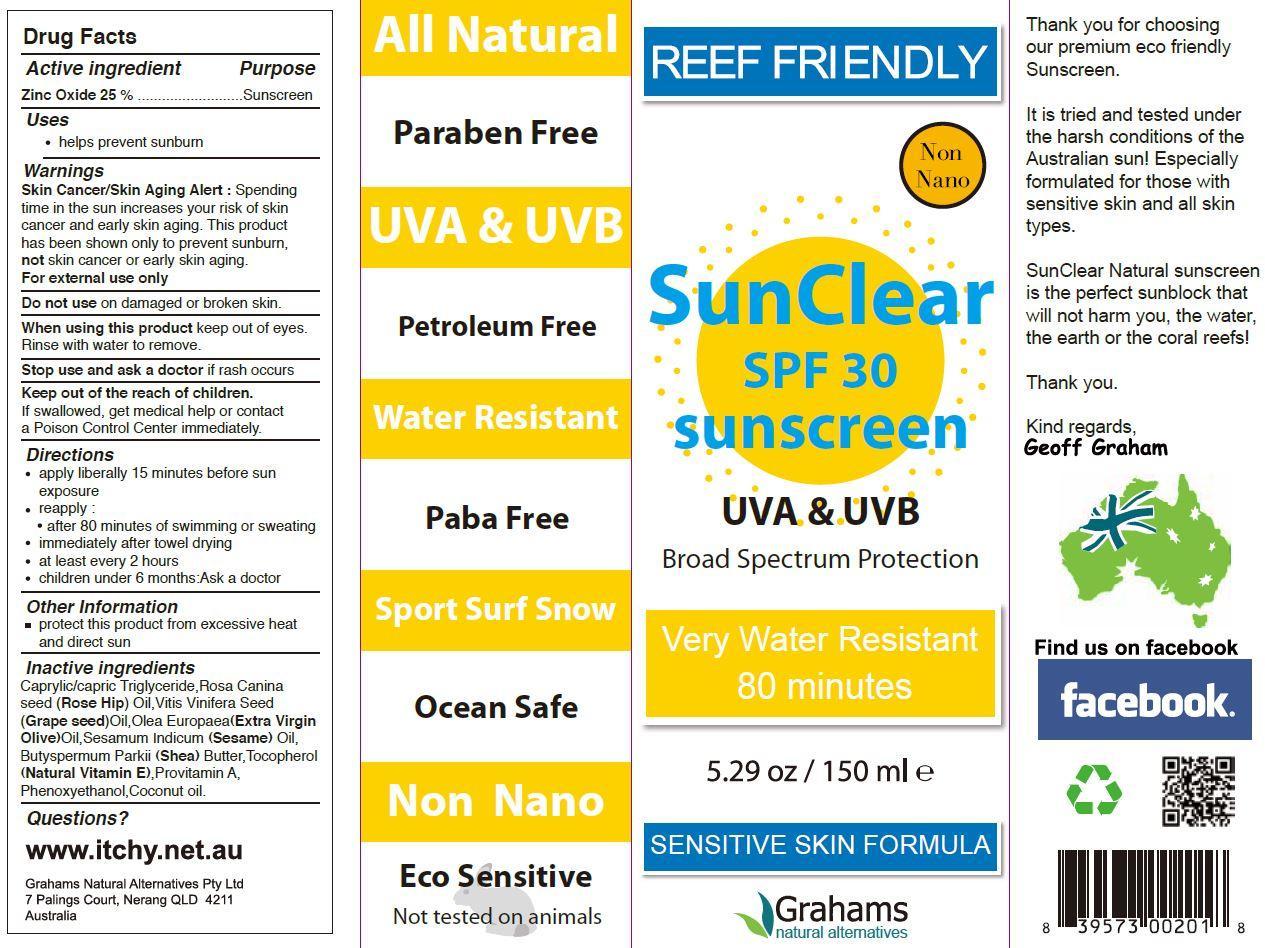 DRUG LABEL: SunClear
NDC: 42387-001 | Form: CREAM
Manufacturer: Grahams Natural Alternatives Pty Ltd
Category: otc | Type: HUMAN OTC DRUG LABEL
Date: 20150826

ACTIVE INGREDIENTS: ZINC OXIDE 25 g/100 g
INACTIVE INGREDIENTS: CAPRYLIC/CAPRIC/LAURIC TRIGLYCERIDE; ROSA CANINA SEED; VITIS VINIFERA SEED; OLIVE OIL; SESAME OIL; SHEA BUTTER; TOCOPHEROL; VITAMIN A; PHENOXYETHANOL; COCONUT OIL

Active Ingredients

Zinc Oxide 25%

Purpose

sunscreen

KEEP OUT OF REACH OF CHILDREN

Keep out of the reach of children. If swallowed, get medical help or contact a poison control center immediately.

Uses

helps prevent sunburn

Directions

apply liberally 15 minutes before sun exposure

reapply:

- after 80 minutes of swimming or sweating
- immediately after towel drying
- at least every 2 hours
- children under 6 months: ask a doctor

Warnings

Skin Cancer/Skin Aging Alert: Spending time in the sun increases your risk of skin cancer and early skin aging. This product has been shown only to prevent sunburn, not skin cancer or early skin aging.

For external use only

Do not use on damaged or broken skin

When using this product keep out of eyes. Rinse with water to remove.

Stop use and ask a doctor if rash occurs

DESCRIPTION

Reef Friendly

Non Nano

SunClear SPF 30 sunscreen

UVA & UVB

Broad Spectrum Protection

Very Water Resistant

80 minutes

Sensitive Skin Formula

Thank you for choosing our premium eco friendly Sunscreen.

It is tried and tested under the harsh conditions of the Australian sun! Especially formulated for those with sensitive skin and all skin types.

SunClear Natural sunscreen is the perfect sunblock that will not harm you, the water, the earth or the coral reefs!

Other Information

protect this product from excessive heat and direct sun

Questions www.itchy.net.au

Made in Australia

Grahams Natural Alternatives Pty Ltd

7 Palings Court, Nerang, QLD 4211 Australia

Inactive Ingredients

caprylic/capric trilglyceride, rosa canina seed (rose hip) oil, vitis vinifera seed (grape seed) oil, olea europaea (extra virgin olive) oil, sesamum indicum (sesame) oil, butyspermum parkii (shea) butter, tocopherol (natural vitamin E), provitamin A, phenoxyethanol, coconut oil.